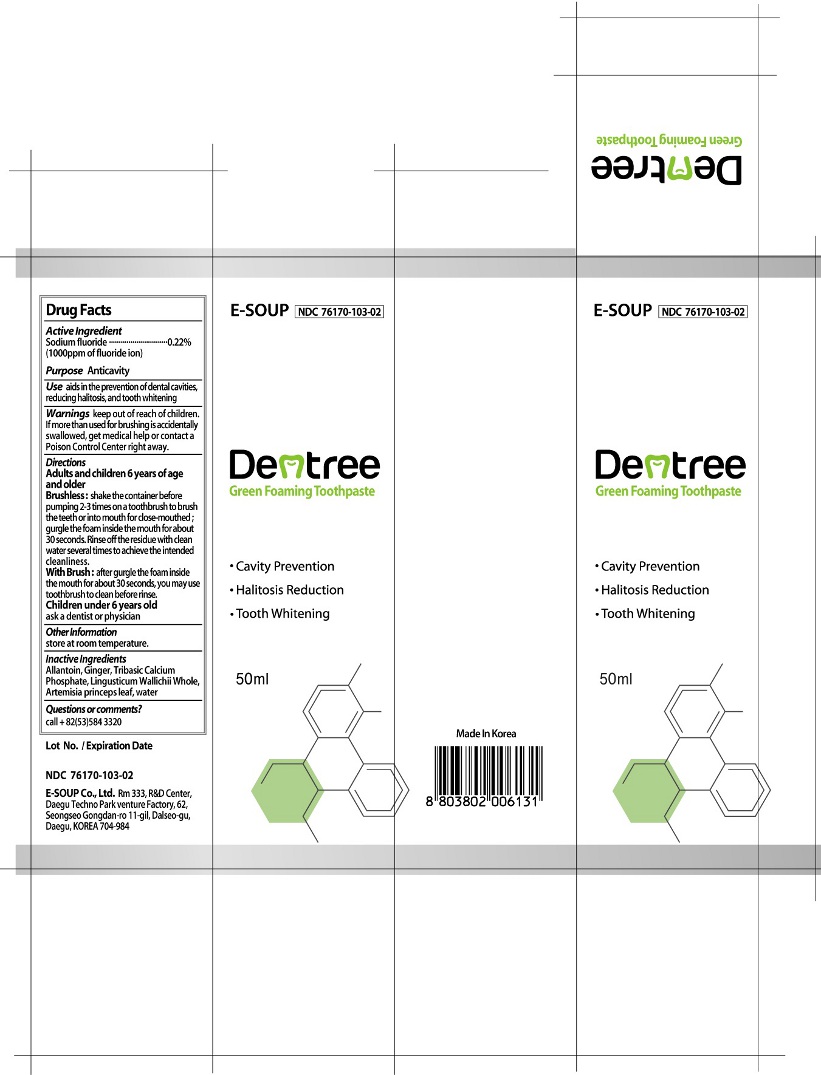 DRUG LABEL: Dentree
NDC: 76170-103 | Form: GEL, DENTIFRICE
Manufacturer: E-SOUP Co., Ltd.
Category: otc | Type: HUMAN OTC DRUG LABEL
Date: 20200420

ACTIVE INGREDIENTS: SODIUM FLUORIDE 0.22 g/100 mL
INACTIVE INGREDIENTS: ALLANTOIN; GINGER; TRIBASIC CALCIUM PHOSPHATE; LIGUSTICUM WALLICHII WHOLE; ARTEMISIA PRINCEPS LEAF; WATER

Drug Facts

Active Ingredient

Sodium fluoride-------------------0.22%
(1000 ppm of fluoride ion)

Purpose

Anticavity

Use

aids in the prevention of dental cavities, reducing halitosis, and tooth whitening

Warnings

keep out of reach of children.
If more than used for brushing is accidentally swallowed, get medical help or contact a Poison Control Center right away.

Directions

Adults and children 6 years of age and older

Brushless: shake the container before pumping 2-3 times on a toothbrush to brush the teeth or into mouth for close-mouthed; gurgle the foam inside the mouth for about 30 seconds. Rinse off the residue with clean water several times to achieve the intended cleanliness.

With Brush: after gurgle the foam inside the mouth for about 30 seconds, you may use toothbrush to clean before rinse.

Children under 6 years old
ask a dentist or physician

Other Information

store at room temperature.

Inactive Ingredients

Allantoin, Ginger, Tribasic Calcium Phosphate, Lingusticum Wallichii Whole, Artemisia princeps leaf, water

Questions or Comments?

call +82(53)584 3320

PRINCIPAL DISPLAY PANEL

E-SOUP
NDC 76170-103-02
Dentree
Green Foaming Toothpaste
• Cavity Prevention
• Halitosis Reduction
• Tooth Whitening
50ml
Lot No. / Expiration Date
E-SOUP Co., Ltd. Rm 333 R&D Center,
Daegu Techno Park venture Factory, 62
Seongseo Gongdan-ro 11-gil, Dalseo-gu,
Daegu, KOREA 704-948
Made in Korea